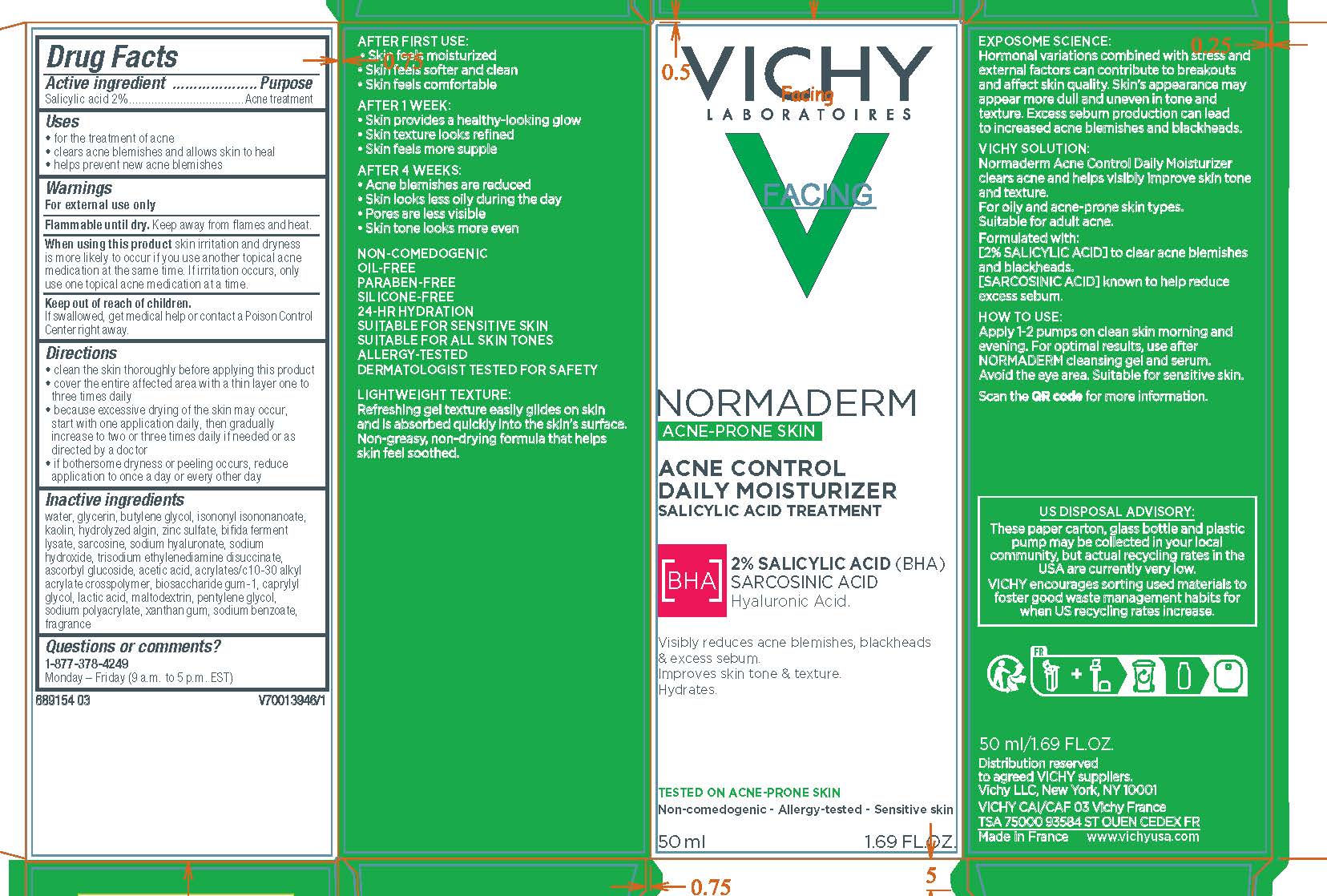 DRUG LABEL: Vichy Laboratoires Normaderm Acne Control Daily Moisturizer
NDC: 49967-660 | Form: GEL
Manufacturer: L'Oreal USA Products Inc
Category: otc | Type: HUMAN OTC DRUG LABEL
Date: 20231211

ACTIVE INGREDIENTS: Salicylic Acid 20 mg/1 mL
INACTIVE INGREDIENTS: WATER; GLYCERIN; ISONONYL ISONONANOATE; BUTYLENE GLYCOL; KAOLIN; ZINC SULFATE; SARCOSINE; HYALURONATE SODIUM; SODIUM HYDROXIDE; TRISODIUM ETHYLENEDIAMINE DISUCCINATE; ASCORBYL GLUCOSIDE; ACETIC ACID; BIOSACCHARIDE GUM-1; CAPRYLYL GLYCOL; LACTIC ACID; MALTODEXTRIN; PENTYLENE GLYCOL; SODIUM POLYACRYLATE (2500000 MW); XANTHAN GUM; SODIUM BENZOATE

Drug Facts

Active ingredient

Salicylic acid...2%

Purpose

Acne treatment

Uses

- for the treatment of acne
- clears acne blemishes and allows skin to heal
- helps prevent new acne blemishes

Warnings

For external use only

Flammable until dry.

Keep away from flames and heat.

When using this product

kin irritation and dryness is more likely to occur if you use another topical acne medication at the same time. if irritation occurs, only use one topical acne medication at a time.

Keep out of reach of children.

If swallowed, get medical help or contact a Poison Control Center right away.

Directions

• clean the skin thoroughly before applying this product
• cover the entire affected area with a thin layer one to three times daily
• because excessive drying of the skin may occur, start with one application daily, then gradually increase to two or three times daily if needed or as directed by a doctor
• if bothersome dryness or peeling occurs, reduce application to once a day or every other day

Inactive ingredients

water, glycerin, butylene glycol, isononyl isononanoate, kaolin, hydrolyzed algin, zinc sulfate, bifida ferment lysate, sarcosine, sodium hyaluronate, sodium hydroxide, trisodium ethylenediamine disuccinate, ascorbyl glucoside, acetic acid, acrylates/c10-30 alkyl acrylate crosspolymer, biosaccharide gum-1, caprylyl glycol, lactic acid, maltodextrin, pentylene glycol, sodium polyacrylate, xanthan gum, sodium benzoate, fragrance

Questions or comments?

Call toll free 1-877-378-4249

Monday - Friday (9 a.m. to 5 p.m. EST)